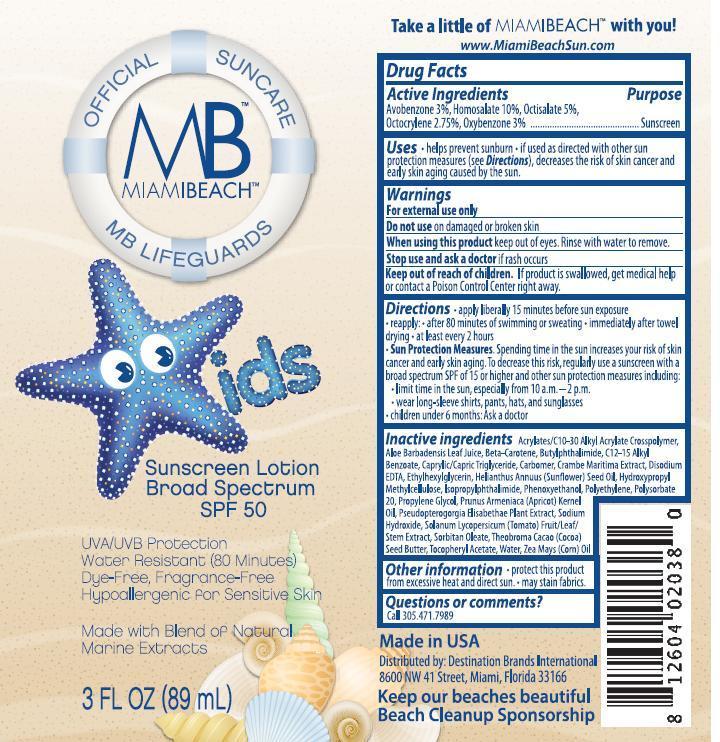 DRUG LABEL: Destination Brands International
NDC: 58443-0190 | Form: LOTION
Manufacturer: Prime Enterprises Inc.
Category: otc | Type: HUMAN OTC DRUG LABEL
Date: 20200117

ACTIVE INGREDIENTS: OXYBENZONE 29.7 mg/1 mL; AVOBENZONE 29.7 mg/1 mL; HOMOSALATE 99 mg/1 mL; OCTISALATE 49.5 mg/1 mL; OCTOCRYLENE 27.2 mg/1 mL
INACTIVE INGREDIENTS: TEA TREE OIL; ETHYLHEXYLGLYCERIN; SUNFLOWER OIL; TRICAPRIN; SODIUM HYDROXIDE; ISOPROPYLPHTHALIMIDE; HYPROMELLOSES; .BETA.-CAROTENE; PHENOXYETHANOL; HIGH DENSITY POLYETHYLENE; CORN OIL; POLYSORBATE 20; PROPYLENE GLYCOL; SORBITAN MONOOLEATE; CARBOMER HOMOPOLYMER TYPE C (ALLYL PENTAERYTHRITOL CROSSLINKED); COCOA BUTTER; ALKYL (C12-15) BENZOATE; N-BUTYLPHTHALIMIDE; TOMATO; APRICOT KERNEL OIL; (C10-C30)ALKYL METHACRYLATE ESTER; ALOE VERA LEAF; ALPHA-TOCOPHEROL ACETATE; EDETATE DISODIUM; WATER; PSEUDOPTEROGORGIA ELISABETHAE; CRAMBE MARITIMA LEAF

Miami Beach Kids SPF 50 Broad Spectrum Lotion Sunscreen

Active Ingredients

Avobenzone 3%

Homosalate 10%

Octisalate 5%

Octocrylene 2.75%

Oxybenzone 3%

PURPOSE

Sunscreen

Uses

- helps prevent sunburn
- if used as directed with other sun protection measures (see Directions), decreases the risk of skin cancer and early skin aging caused by the sun

WARNINGS

For external use only.

Do not use on damaged or broken skin

When using this product keep out of eyes. Rinse with water to remove.

Stop use and ask a doctor if rash occurs

Keep out of reach of children. If product is swallowed, get medical help or contact a Poison Control Center right away.

Directions

- apply liberally 15 minutes before sun exposure
- reapply:
- after 80 minutes of swimming or sweating
- immediately after towel drying
- at least every 2 hours
- Sun Protection Measures. Spending time in the sun increases your risk of skin cancer and early skin aging. To decrease this risk, regularly use a sunscreen with broad spectrum SPF of 15 or higher and other sun protection measures including:
- limit time in the sun, especially from 10 a.m. – 2 p.m.
- wear long-sleeve shirts, pants, hats, and sunglasses
- children under 6 months: Ask a doctor

INACTIVE INGREDIENT

Acrylates/C10-30 Alkyl Acrylate Crosspolymer, Aloe Barbadensis Leaf Juice, Beta-Carotene, Butylphthalimide, C12-15 Alkyl Benzoate, Caprylic/Capric Triglyceride, Carbomer, Crambe Maritima Extract, Disodium EDTA, Ethylhexylglycerin, Helianthus Annuus (Sunflower) Seed Oil, Hydroxypropyl Methylcellulose, Isopropylphthalimide, Phenoxyethanol, Polyethylene, Polysorbate 20, Propylene Glycol, Prunus Armeniaca (Apricot) Kernel Oil, Pseudopterogorgia Elisabethae Plant Extract, Sodium Hydroxide, Solanum Lycopersicum (Tomato) Fruit/Leaf/Stem Extract, Sorbitan Oleate, Theobroma Cacao (Cocoa) Seed Butter, Tocopheryl Acetate, Water (Aqua), Zea Mays (Corn) Oil

Other Information

- protect this product from excesive heat and direct sun
- may stain fabrics.

Questions or Comments?

Call 305.471.7989